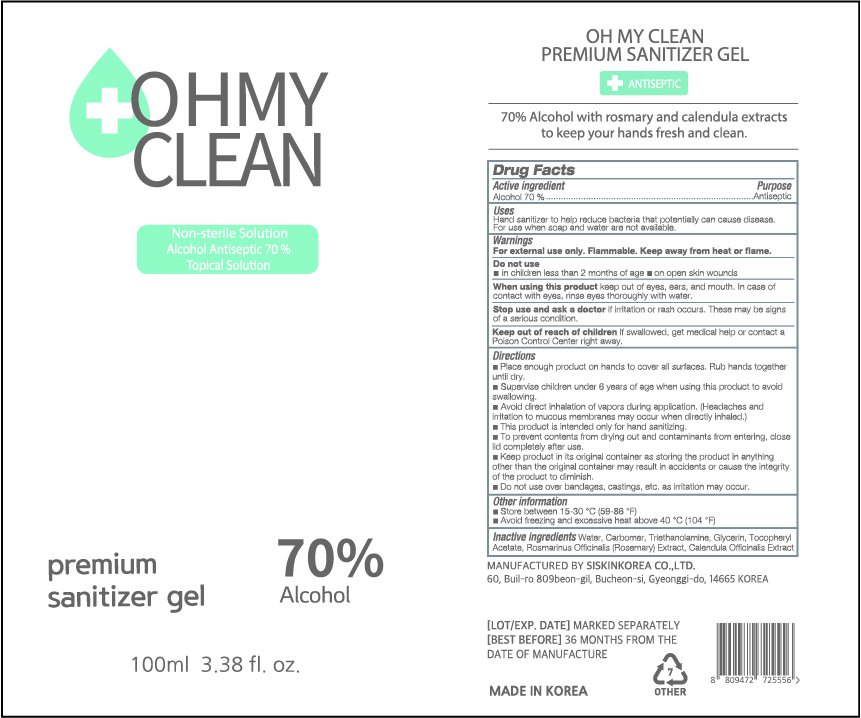 DRUG LABEL: OH MY CLEAN PREMIUM SANITIZER Gel
NDC: 74514-1070 | Form: GEL
Manufacturer: SISKINKOREA CO.,LTD.
Category: otc | Type: HUMAN OTC DRUG LABEL
Date: 20200515

ACTIVE INGREDIENTS: ALCOHOL 70 mL/100 mL
INACTIVE INGREDIENTS: TROLAMINE; GLYCERIN; .ALPHA.-TOCOPHEROL ACETATE; CALENDULA OFFICINALIS WHOLE; WATER; ROSEMARY; CARBOMER HOMOPOLYMER, UNSPECIFIED TYPE

[Packaging change] 100ml_70%_gel_OH MY CLEAN PREMIUM SANITIZER GEL [74514-0170-1] -> 74514-1070-1